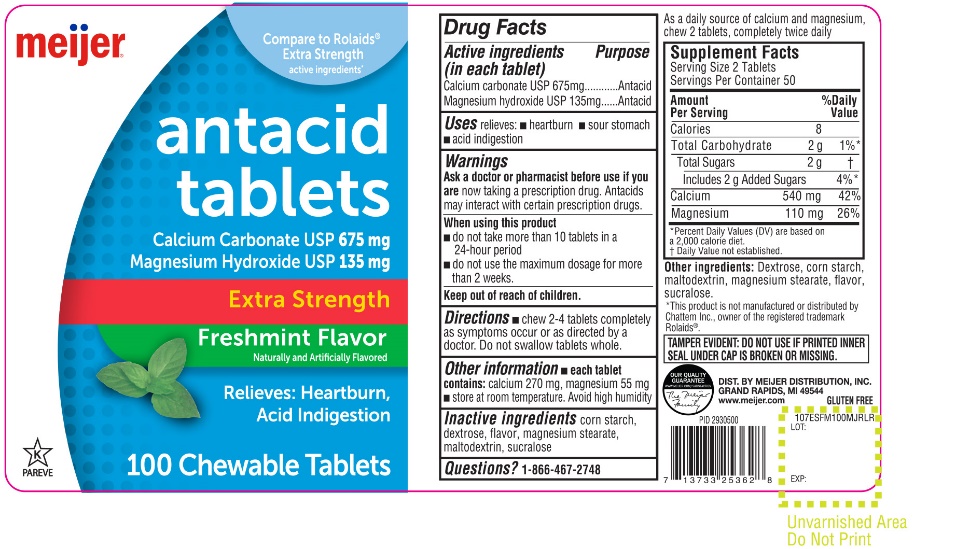 DRUG LABEL: Meijer Extra Strength

NDC: 41250-978 | Form: TABLET, CHEWABLE
Manufacturer: MEIJER DISTRIBUTION INC
Category: otc | Type: HUMAN OTC DRUG LABEL
Date: 20251024

ACTIVE INGREDIENTS: CALCIUM CARBONATE 675 mg/1 1; MAGNESIUM HYDROXIDE 135 mg/1 1
INACTIVE INGREDIENTS: STARCH, CORN; DEXTROSE, UNSPECIFIED FORM; MAGNESIUM STEARATE; MALTODEXTRIN; SUCRALOSE

Meijer Extra Strength Antacid Tablets Freshmint Flavor

Drug Facts

Active ingredients

(in each tablet)
Calcium Carbonate USP 675 mg
Magnesium hydroxide USP 135 mg

Purpose

Antacid

Antacid

Uses

relieves:

- heartburn
- sour stomach
- acid indigestion

Warnings

Ask a doctor or pharmacist before use if you are

now taking a prescription drug. Antacids may interact with certain prescription drugs.

When using this product

- do not take more than 10 tablets in a 24-hour period,
- do not use the maximum dosage for more than 2 weeks

Directions

- chew 2-4 tablets completely as symptoms occur or as directed by a doctor. Do not swallow tablets whole.

Other information

- each tablet contains:calcium 270 mg, magnesium 55 mg
- store at room temperature
- Avoid high humidity.

Inactive ingredients

corn starch, dextrose, flavor, magnesium stearate, maltodextrin, sucralose.

Questions?

1-866-467-2748

PRINCIPAL DISPLAY PANEL

Meijer®

NDC# 41250-978-10

Compare to Rolaids® Extra Strength active ingredients*

Antacid Tablets

Calcium Carbonate USP 675 mg

Magnesium Hydroxide USP 135 mg

Extra Strength

Freshmint Flavor

Naturally and Artificially Flavored

Relieves: Heartburn, Acid Indigestion

100 CHEWABLE TABLETS

GLUTEN FREE

K PAREVE

OUR QUALITY GURANTEE

WWW.MEIJER.COM/SATISFACTION

TAMPER EVIDENT: DO NOT USE IF PRINTED INNER SEAL IS BROKEN OR MISSING

*This product is not manufactured or distributed by Chattem Inc., owner of the registered trademark Rolaids®

DIST. BY MEIJER DISTRIBUTION, INC.

GRAND RAPIDS, MI 49544

www.meijer.com